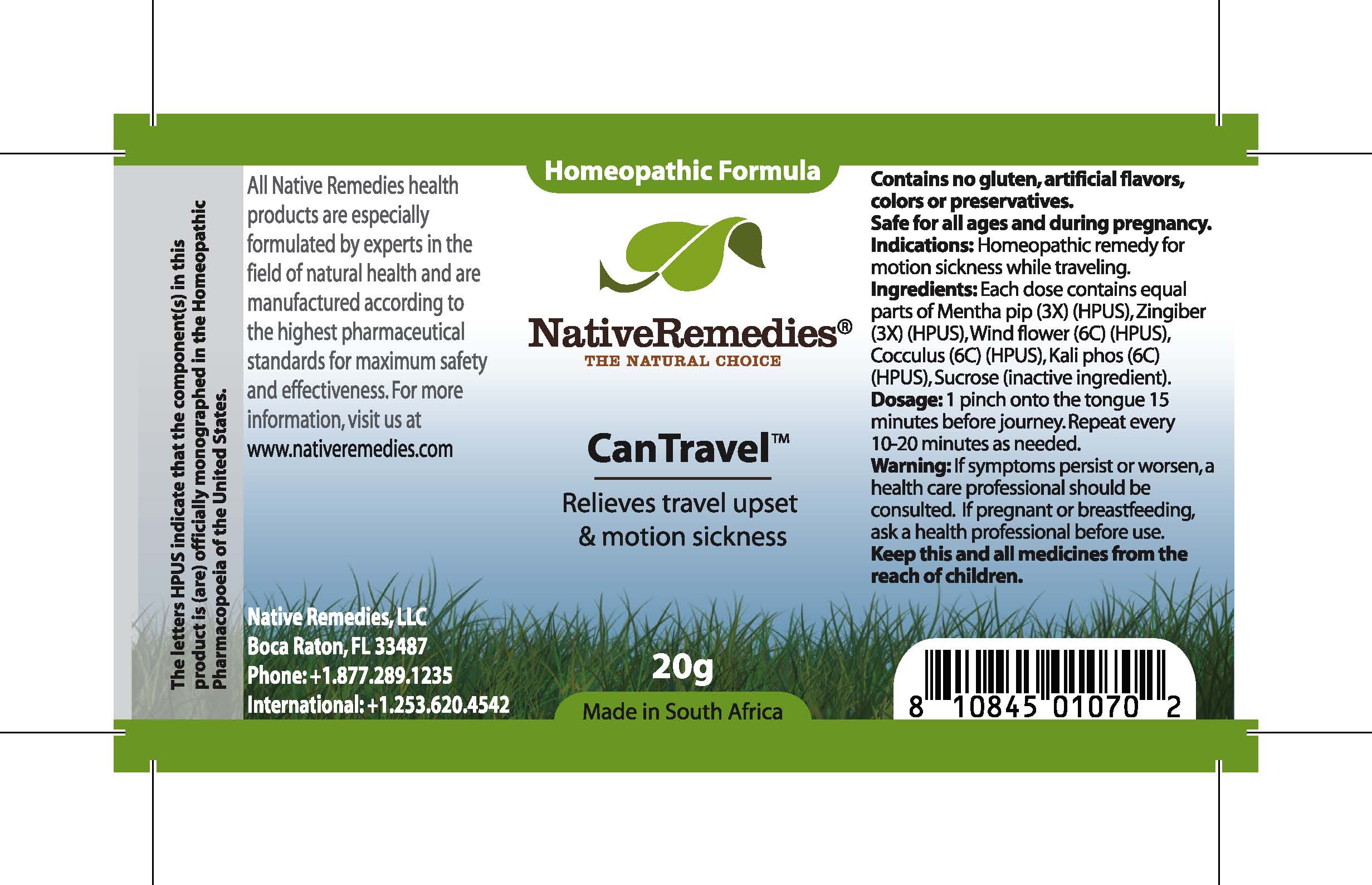 DRUG LABEL: CanTravel
NDC: 68647-160 | Form: GRANULE
Manufacturer: Feelgood Health
Category: homeopathic | Type: HUMAN OTC DRUG LABEL
Date: 20100721

ACTIVE INGREDIENTS: PEPPERMINT 3 [hp_X]/50 mg; CARDAMOM 3 [hp_X]/50 mg; PULSATILLA PATENS 6 [hp_C]/50 mg; ANAMIRTA COCCULUS SEED 6 [hp_C]/50 mg; POTASSIUM PHOSPHATE, DIBASIC 6 [hp_C]/50 mg
INACTIVE INGREDIENTS: SUCROSE

CANTRAVEL

DESCRIPTION

Relieves travel upset and motion sickness

Indications: Homeopathic remedy for motion sickness while traveling.

DOSAGE AND ADMINISTRATION

Dosage: 1 pinch onto the tongue 15 minutes before journey. Repeat every 10-20 minutes as needed.

GENERAL PRECAUTIONS

Caution: If symptoms persist or worsen, a health care professional should be consulted. Keep this and all medicines from the reach of children.

ACTIVE INGREDIENT

Ingredients: Each dose contains equal parts of Mentha pip (3X) (HPUS), Zingiber (3X) (HPUS), Pulsatilla (6C) (HPUS), Cocculus (6C) (HPUS), Kali phos (6C) (HPUS)

Sucrose (inactive ingredient).

PREGNANCY

If pregnant or breastfeeding, ask a health professional before use.

USER SAFETY WARNINGS

Contains no gluten, artificial flavors, colors or preservatives. Safe for all ages and during pregnancy.

PATIENT COUNSELING INFORMATION

All Native Remedies health products are especially formulated by experts in the field of natural health and are manufactured according to the highest pharmaceutical standards for maximum safety and effectiveness. For more information, visit us at www.nativeremedies.com

Distributed by

Native Remedies, LLC

6531 Park of Commerce Blvd.

Suite 160

Boca Raton, FL 33487

Phone: 1.877.289.1235

International: + 1.561.999.8857

The letters HPUS indicate that the component(s) in this product is (are) officially monographed in the Homeopathic Pharmacopoeia of the United States.